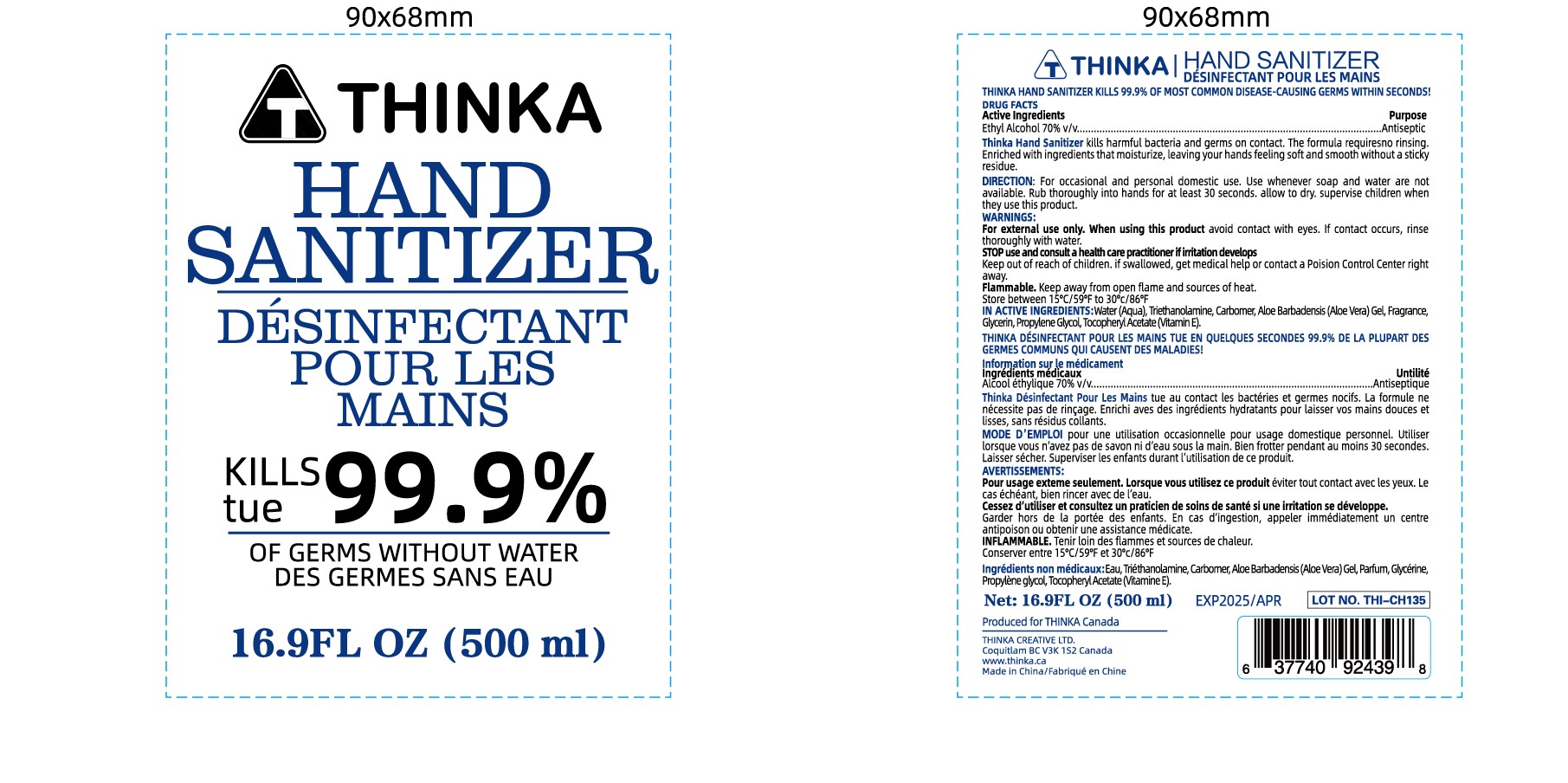 DRUG LABEL: Thinka Hand Sanitizer
NDC: 76114-009 | Form: SOLUTION
Manufacturer: Zhejiang Aidi Cosmetics Co., Ltd
Category: otc | Type: HUMAN OTC DRUG LABEL
Date: 20200512

ACTIVE INGREDIENTS: ALCOHOL 70 mL/100 mL
INACTIVE INGREDIENTS: GLYCERIN; WATER; CARBOMER 934; PROPYLENE GLYCOL; ALPHA-TOCOPHEROL ACETATE; TROLAMINE; ALOE VERA WHOLE

NA

Active Ingredient(s)

Ethyl Alcohol 70% v/v

Purpose

Antispetic

Use

Thinka Hand Sanitizer kills harmful bacteria and germs on contact. The formula requires no rinsing. Enriched with ingredients that moisturize, leaving your hands feels soft and smooth without a sticky residue.

Warnings

For external use only

Flammable. Keep away from flame and sources of heat

When using this product keep out of eyes. If contact occurs, rinse thoroughly with water.

Stop use and consult a healthcare practitioner if irritation develops

Keep out of reach of children. If swallowed, get medical help or contact a Poison Control Center right away.

Directions

For occational and personal domestic use. Use whenever soap and water is not available

Rub thoroughly into hand for atleast 30 seconds, allow to dry

Supervise children when they use this product

Other information

Store between 15-30 C (59 to 86F)

Inactive ingredients

Water, triethanolamine, glycerin, propylene glycol, tocopheryl acetate (Vitamin E), aloe barbadensis gel, carbomer, fragrance